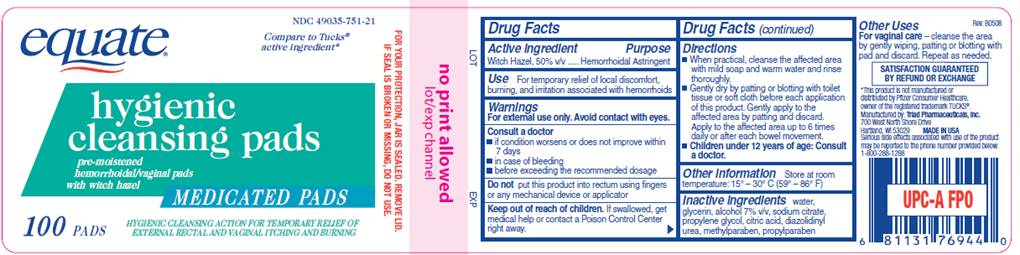 DRUG LABEL: Hygienic Cleansing Pad
NDC: 49035-751 | Form: SOLUTION
Manufacturer: Wal-Mart Stores Inc
Category: otc | Type: HUMAN OTC DRUG LABEL
Date: 20091229

ACTIVE INGREDIENTS: witch hazel 0.50 mL/1 mL
INACTIVE INGREDIENTS: citric acid monohydrate; diazolidinylurea; glycerin; methylparaben; propylene glycol; propylparaben; sodium citrate; water

DRUG FACTS

ACTIVE INGREDIENT

Witch Hazel 50% v/v

PURPOSE

Hemorrhoidal Astringent

USE

For temporary relief of local discomfort, burning, and irritation associated with hemorrhoids

WARNINGS

For external use only. Avoid contact with eyes.

Consult a doctor

- if condition worsens or does not improve within 7 days
- in case of bleeding
- before exceeding the recommended dosage

Do not

put this product into rectum using fingers or any mechanical device or applicator

Keep out of reach of children

If swallowed, get medical help or contact a Poison Control Center right away.

DIRECTIONS

- When practical, cleanse the affected area with mild soap and warm water and rinse thoroughly.
- Gently dry by patting or blotting with toilet tissue or soft cloth before each application of this product. Gently apply to the affected area by patting and then discard. Apply to the affected area up to 6 times daily or after each bowel movement.
- Children under 12 years of age: consult a doctor.

OTHER INFORMATION

Store at room temperature: 15°- 30° C (59° - 86° F)

OTHER USES

For vaginal care - cleanse the area by gently wiping, patting or blotting with pad and discard. Repeat as needed.

INACTIVE INGREDIENTS

water, glycerin, alcohol 7% v/v, sodium citrate, propylene glycol, citric acid, diazolidinyl urea, methylparaben, propylparaben

LABEL INFORMATION

NDC 49035-751-21

EQUATE

Compare to Tucks® active ingredient*
Hygienic Cleansing Pads
pre-moistened hemorrhoidal/vaginal pads with witch hazel
MEDICATED PADS
100 PADS
Hygienic cleansing action for temporary relief of external rectal and vaginal itching and burning
For your protection, jar is sealed. Remove lid. If seal is broken or missing, do not use.
*This product is not manufactured or distributed by Pfizer Consumer Healthcare, owner of the registered trademark TUCKS®.
Manufactured by: Triad Pharmaceuticals, Inc. 700 West North Shore Drive, Hartland, WI 53029
Serious side effects associated with use of this product can be reported to the phone number provided below.
1-800-288-1288